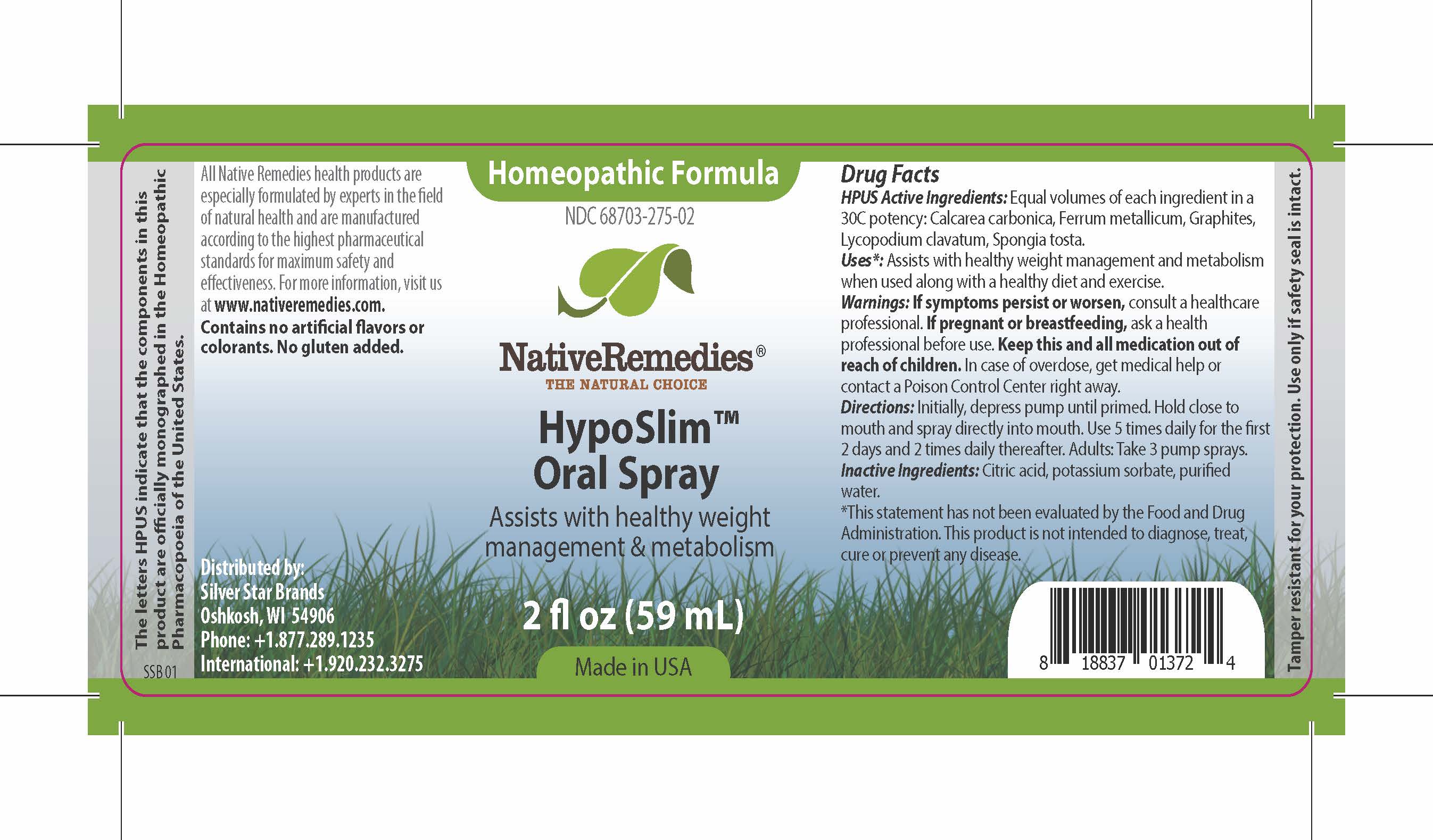 DRUG LABEL: HypoSlim
NDC: 68703-275 | Form: SPRAY
Manufacturer: Silver Star Brands
Category: homeopathic | Type: HUMAN OTC DRUG LABEL
Date: 20170206

ACTIVE INGREDIENTS: SPONGIA OFFICINALIS WHOLE 30 [hp_C]/59 mL; CALCIUM CARBONATE 30 [hp_C]/59 mL; IRON DEXTRAN 30 [hp_C]/59 mL; GRAPHITE 30 [hp_C]/59 mL; LYCOPODIUM CLAVATUM WHOLE 30 [hp_C]/59 mL
INACTIVE INGREDIENTS: POTASSIUM SORBATE; ANHYDROUS CITRIC ACID; WATER

NativeRemedies® HypoSlim™ Oral Spray

HPUS Active Ingredients:

Equal volumes of each ingredient in a 30C potency: Calcarea carbonica, Ferrum metallicum, Graphites, Lycopodium clavatum, Spongia tosta.

Uses*:

Assists with healthy weight management and metabolism when used along with a healthy diet and exercise.

*This statement has not been evaluated by the Food and Drug Administration. This product is not intended to diagnose, treat, cure or prevent any disease.

Warnings:

If symptoms persist or worsen, consult a healthcare professional. If pregnant or breastfeeding, ask a health professional before use. Keep this and all medication out of reach of children. In case of overdose, get medical help or contact a Poison Control Center right away.

Directions:

Initially, depress pump until primed. Hold close to mouth and spray directly into mouth. Use 5 times daily for the first 2 days and 2 times daily thereafter. Adults: Take 3 pump sprays.

Inactive Ingredients:

Citric acid, potassium sorbate, purified water.

OTHER SAFETY INFORMATION

All Native Remedies health products are especially formulated by experts in the field of natural heatlh and are manufactured according to the highest pharmaceutical standards for maximum safety and effectiveness. For more information, visit us at www.nativeremedies.com. Contains no artificial flavors or colorants. No gluten added.

KEEP OUT OF REACH OF CHILDREN

Keep this and all medication out of reach of children. In case of overdose, get medical help or contact a Poison Control Center right away.

PREGNANCY OR BREAST FEEDING

If pregnant or breastfeeding, ask a health professional before use.

PURPOSE

Assists with healthy weight management & metabolism